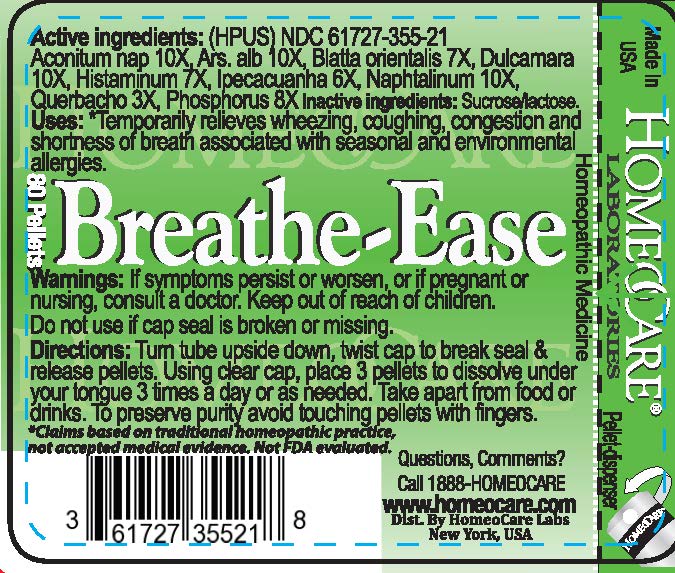 DRUG LABEL: Breathe-Ease
NDC: 61727-355 | Form: PELLET
Manufacturer: Homeocare Laboratories
Category: homeopathic | Type: HUMAN OTC DRUG LABEL
Date: 20210407

ACTIVE INGREDIENTS: SOLANUM DULCAMARA TOP 10 [hp_X]/4 g; NAPHTHALENE 10 [hp_X]/4 g; PHOSPHORUS 8 [hp_X]/4 g; ACONITUM NAPELLUS 10 [hp_X]/4 g; BLATTA ORIENTALIS 7 [hp_X]/4 g; ARSENIC CATION (3+) 10 [hp_X]/4 g; HISTAMINE 7 [hp_X]/4 g; IPECAC 6 [hp_X]/4 g; QUEBRACHO BARK 3 [hp_X]/4 g
INACTIVE INGREDIENTS: SUCROSE; LACTOSE, UNSPECIFIED FORM

Breathe-Ease

Active Ingredients

Aconitum nap 10X, Ars. alb. 10X, Blatta orientalis 7X, Dulcamara 10X, Histaminum 7X, Ipecacuanha 6X, Naphtalinum 10X, Querbacho 3X, Phosphorus 8X.

Uses

Temporarily relieves wheezing, coughing, congestion and shortness of breath associated with seasonal and environmental allergies.

Keep Out of Reach of Children

Directions

Turn tube upside down, twist cap to break seal & release pellets. Using clear cap, place 3 pellets to dissolve under your tongue 3 times a day or as needed. Take apart from food or drinks. To preserve purity avoid touching pellets with fingers.

Warnings

If symptoms persist or worsen, or if pregnant or nursing, consult a doctor. Do not use if cap seal is broken or missing.

Inactive Ingredients

Sucrose, lactose

Dosage & Administration

Turn tube upside down, twist cap to break seal & release pellets. Using clear cap, place 3 pellets to dissolve under your tongue 3 times a day or as needed. Take apart from food or drinks. To preserve purity avoid touching pellets with fingers.